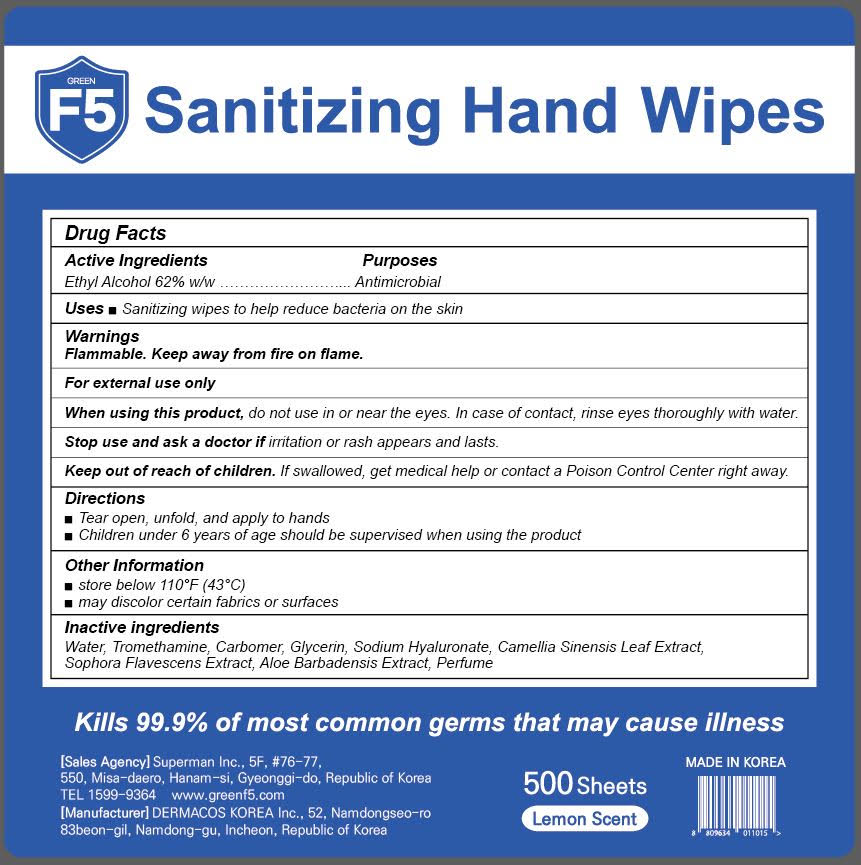 DRUG LABEL: Green F5 Sanitizing Hand Wipes
NDC: 81711-001 | Form: CLOTH
Manufacturer: SUPERMAN.CO.,LTD
Category: otc | Type: HUMAN OTC DRUG LABEL
Date: 20210327

ACTIVE INGREDIENTS: ALCOHOL 0.62 g/1 g
INACTIVE INGREDIENTS: WATER; TROMETHAMINE; CARBOMER HOMOPOLYMER, UNSPECIFIED TYPE; GLYCERIN; HYALURONATE SODIUM; GREEN TEA LEAF; SOPHORA FLAVESCENS ROOT; ALOE VERA LEAF

81711-001_Green F5 Sanitizing Hand Wipes

Active ingredient

Ethyl alcohol 62%

Purpose

Antimicrobial

Use

- Sanitizing wipes to help reduce bacterial on the skin

Warnings

Flammable. Keep away from fire or flame.

For external use only

When using this product do not use in or near the eyes. In case of contact, rinse eyes thoroughly with water.

Stop use and ask a doctor if irritation or rash appears and lasts

Keep out of reach of children. If swallowed, get medical help or contact a Poison Control Center right away.

Directions

- Tear Open, unfold and apply to hands
- Children under 6 years of age should be supervised when using this product

Other information

- Store below 110°F (43°C)
- May discolor certain fabrics or surfaces

Inactive ingredients

Water, Tromethamine, Carbomer, Glycerin, Sodium Hyaluronate, Camellia Sinensis Leaf Extract, Sophora Flavescens Extract, Aloe Barbadensis Extract, Perfume